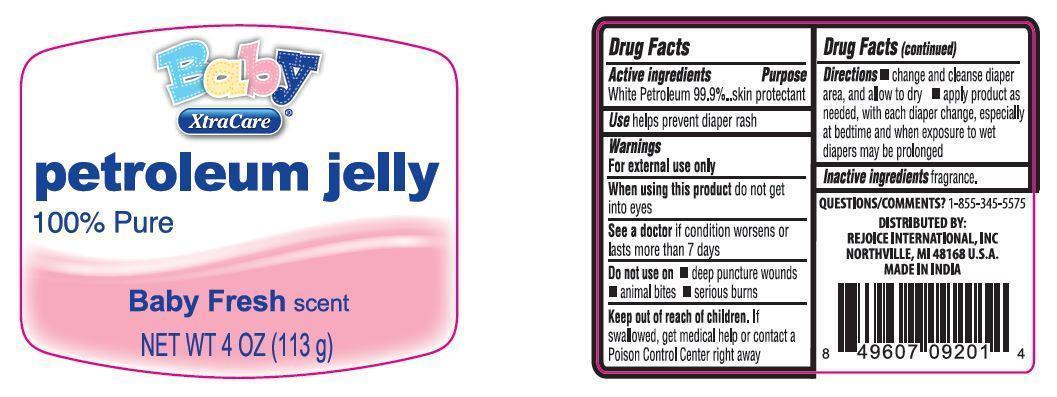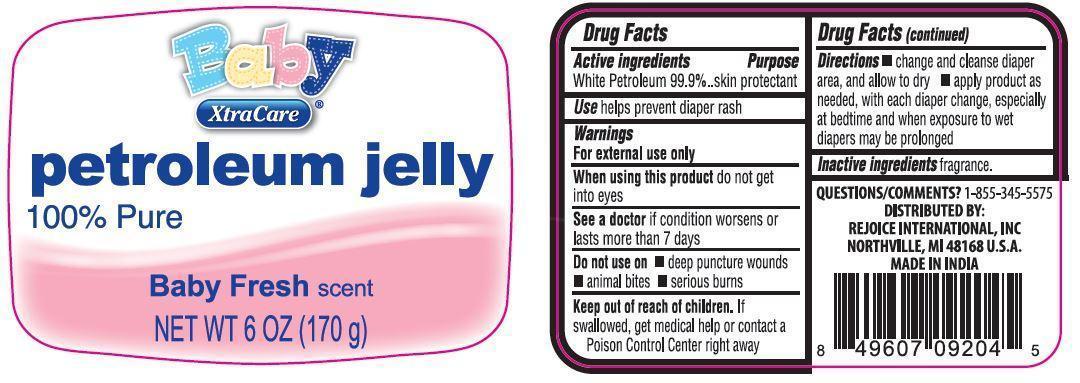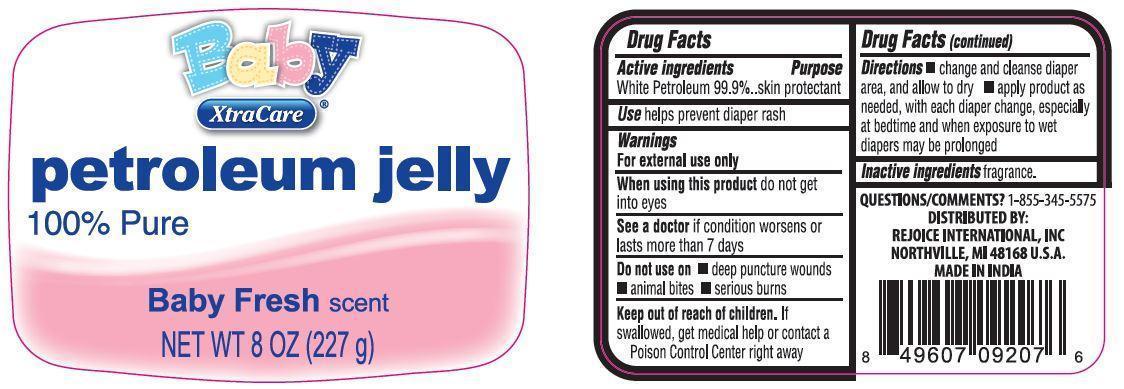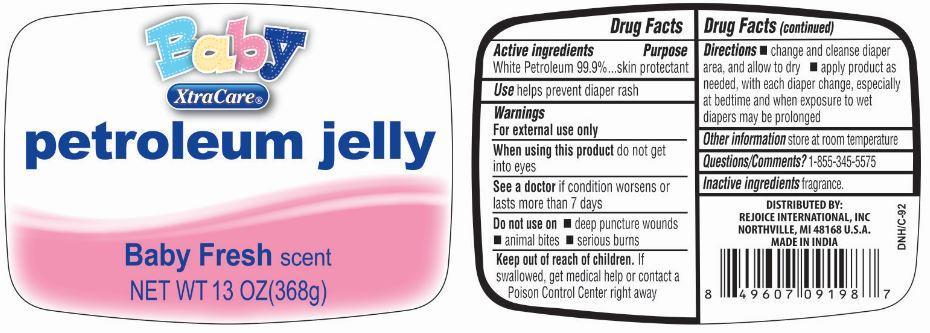 DRUG LABEL: Baby Petroleum Jelly
NDC: 57337-076 | Form: CREAM
Manufacturer: Rejoice International Inc.
Category: otc | Type: HUMAN OTC DRUG LABEL
Date: 20241219

ACTIVE INGREDIENTS: PETROLATUM 99 g/100 g
INACTIVE INGREDIENTS: WATER

Baby Petroleum Jelly

Active Ingredients Purpose

White Petroleum 99.9% ...... skin protectant

Uses

temporarily protects and helps relieve chapped or cracked skin and lips

Keep out of reach of children. If swallowed, get medical help or contact a Poison Control Center right away.

INDICATIONS AND USAGE

XtraCare

100% Pure Petroleum Jelly

Baby Fresh Scent

Directions

- change and cleanse diaper area, and allow to dry
- apply product as needed, with each diaper change, especially at bedtime and when exposure to wet diapers may be prolonged

Warnings

For external use only

When using this product do not get into eyes

See a doctor if condition lasts more than 7 days

Do not use on

- deep puncture wounds
- animal bites
- serious burns

Inactive ingredients fragrance